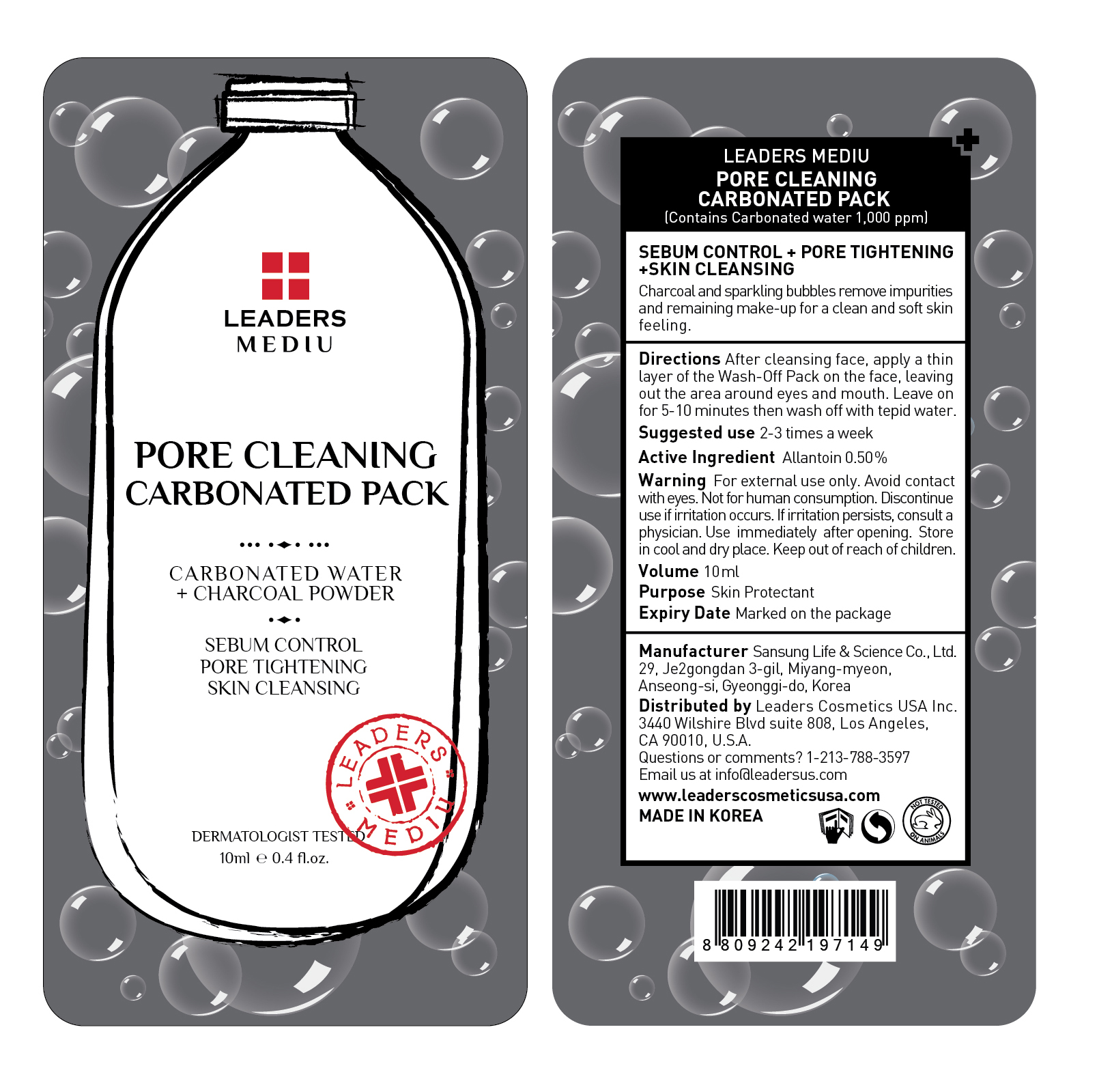 DRUG LABEL: Leaders Mediu Pore Cleaning Carbonated Pack
NDC: 69424-480 | Form: GEL
Manufacturer: SANSUNG LIFE & SCIENCE CO., LTD.
Category: otc | Type: HUMAN OTC DRUG LABEL
Date: 20160201

ACTIVE INGREDIENTS: Allantoin 50 mg/10 mL
INACTIVE INGREDIENTS: Water; Cocamidopropyl Betaine

ACTIVE INGREDIENT

Active Ingredient: Allantoin 0.50%

INACTIVE INGREDIENT

Inactive Ingredients: Water, Cocamidopropyl Betaine, Acrylates Copolymer, Methyl Perfluorobutyl Ether, Methyl Perfluoroisobutyl Ether, Glycerin, Sodium Laureth Sulfate, Butylene Glycol, Dipropylene Glycol, Disodium Cocoamphodiacetate, Kaolin, Bentonite, Lauramide DEA, Titanium Dioxide, Charcoal Powder, Xanthan gum, TEA-Cocoyl Glutamate, Lactobacillus/Lycium chinense fruit extract ferment filtrate, Lactobacillus/Aloe barbadensis ferment filtrate, Potassium Hydroxide, Disodium EDTA, Lactobacillus/Rice ferment filtrate, Carbonated Water, Phenoxyethanol, Chlorphenesin, Fragrance

PURPOSE

Purpose: Skin Protectant

WARNINGS

Warnings: For external use only. Avoid contact with eyes. Not for human consumption. Discontinue use if irritation occurs. If irritation persists, consult a physician.

Use immediately after opening. Store in cool and dry place. Keep out of reach of children.

KEEP OUT OF REACH OF CHILDREN

Directions

Directions: After cleansing face, apply a thin layer of the Wash-Off Pack on the face, leaving out the area around eyes and mouth. Leave on for 5-10 minutes then wash off with tepid water. *Suggested use is 2-3 times a week.

Directions

Directions: After cleansing face, apply a thin layer of the Wash-Off Pack on the face, leaving out the area around eyes and mouth. Leave on for 5-10 minutes then wash off with tepid water. *Suggested use is 2-3 times a week.